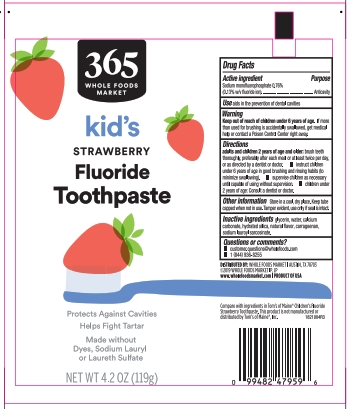 DRUG LABEL: 365 Everyday Value
NDC: 42681-5276 | Form: PASTE, DENTIFRICE
Manufacturer: Whole Foods Market, Inc.
Category: otc | Type: HUMAN OTC DRUG LABEL
Date: 20251112

ACTIVE INGREDIENTS: SODIUM MONOFLUOROPHOSPHATE 0.13 g/100 g
INACTIVE INGREDIENTS: GLYCERIN; CARRAGEENAN; CALCIUM CARBONATE; HYDRATED SILICA; WATER; SODIUM LAUROYL SARCOSINATE

5820004 365 Everyday Value Kids Fluoride Toothpaste Strawberry

Drug Facts

Active ingredient

Sodium monofluorophosphate 0.76%

Purpose

Anticavity

Use

aids in the prevention of dental cavities

Warning

Keep out of reach of children under 6 years of age. If more than used for brushing is accidentally swallowed, get medical help or contact a Poison Control Center right away.

Directions

Adults and children 2 years of age and older: brush teeth thorughly preferably after each meal or at least twice a day, or as directed by a dentist or doctor.

- Instruct children under 6 years of age in good brushing and rinsing habits (to minimize swallowing)
- Supervise children as necessary until capable of using without supervision
- Children under 2 years of age: consult a dentist or doctor

INACTIVE INGREDIENT

Inactive ingredients glycerin, water, calcium carbonate, hydrated silica, carrageenan, sodium sauroyl sarcosinate, natural flavors.

Other information

Store in a cool dry place. Keep tube capped when not in use.

Tamper evident, use only if seal is intact.

Questions or comments?

- customer.questions@wholefoods.com
- 1 (844) 936-8255

DISTRIBUTED BY:

WHOLE FOODS MARKET

AUSTIN, TX 78703

www.wholefoods.com

PRODUCT OF USA

Principal Display Panel

kid's fluoride toothpaste

strawberry

PROTECTS AGAINST CAVITIES

HELPS FIGHT TARTAR

MADE WITHOUT DYES

MADE WITHOUT SODIUM LAURYL OR LAURETH SULFATE

NET WT 4.2 OZ (119g)